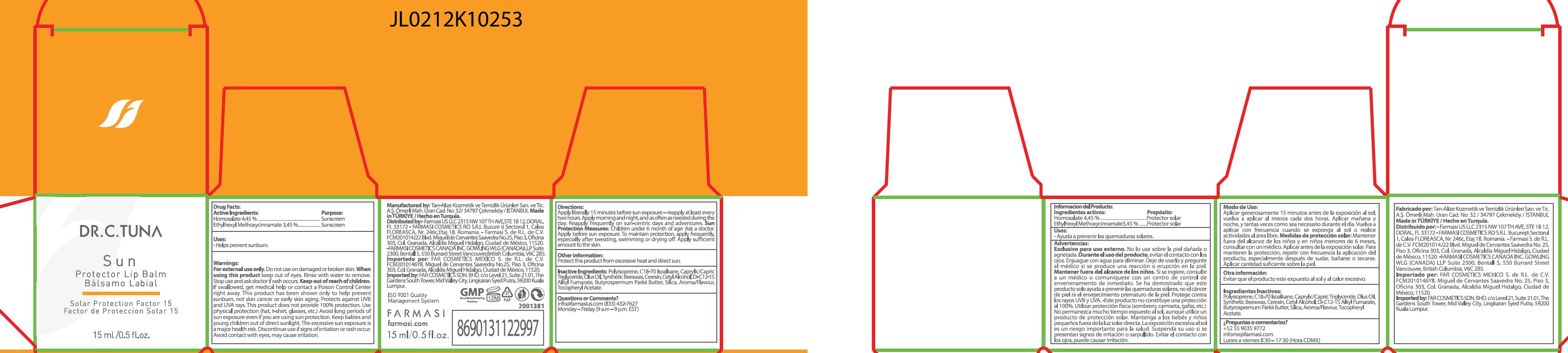 DRUG LABEL: Dr. C. TUNA SUN PROTECTOR LIP BALM SPF 15
NDC: 74690-030 | Form: CREAM
Manufacturer: FARMASI US LLC
Category: otc | Type: HUMAN OTC DRUG LABEL
Date: 20260109

ACTIVE INGREDIENTS: HOMOSALATE 44.5 mg/1 mL; OCTINOXATE 34.5 mg/1 mL
INACTIVE INGREDIENTS: MEDIUM-CHAIN TRIGLYCERIDES; SYNTHETIC BEESWAX; CERESIN; CETYL ALCOHOL; DI-C12-15 ALKYL FUMARATE; SILICON DIOXIDE; .ALPHA.-TOCOPHEROL ACETATE

Dr. C. TUNA SUN PROTECTOR LIP BALM SPF 15

Active Ingredients:

Homosalate 4,45 %

Ethylhexyl Methoxycinnamate 3,45 %

Purpose:

Sunscreen

Uses:

- Helps prevent sunburn.

Warnings:

For external use only.

Do not use

on damaged or broken skin.

undefined

keep out of eyes. Rinse with water to remove.

Stop use and ask a doctor

if rash occurs.

Keep out of reach of children.

If swallowed, get medical help or contact a Poison Control Center right away. This product has been shown only to help prevent sunburn, not skin cancer or early skin aging. Protects against UVB and UVA rays. This product does not provide 100% protection. Use physical protection (hat, t-shirt, glasses, etc.) Avoid long periods of sun exposure even if you are using sun protection. Keep babies and young children out of direct sunlight. The excessive sun exposure is a major health risk, Discontinue use if signs of irritation or rash occur. Aovid contact with eyes, may cause irritation.

Directions:

Apply liberally 15 minutes before sun exposure - reapply at least every two hours. Apply morning and night, and as often as needed during the day. Reapply frequently on sun-centric days, and adventures. Children under 6 months of age: Ask a doctor. Apply before sun exposure. To maintain protection, apply frequently, especially after sweating, swimming or drying off. Apply sufficient amount to the skin. Sun Protection Measures:

Other information:

Protect this product from excessive heat and direct sun.

Inactive Ingredients:

Polyisoprene, C18-70 Isoalkane, Caprylic/Capric Triglyceride, Olus Oil, Synthetic Beeswax, Ceresin, Cetyl Alcohol, Di-C12-15 Alkyl Fumarate, Butyrospermum Parkii Butter, Silica, Aroma/Flavour, Tocopheryl Acetate.

Questions or Comments?

info@farmasius.com (833) 432-7627 Monday - Friday (9 a.m. -9 p.m. EST)